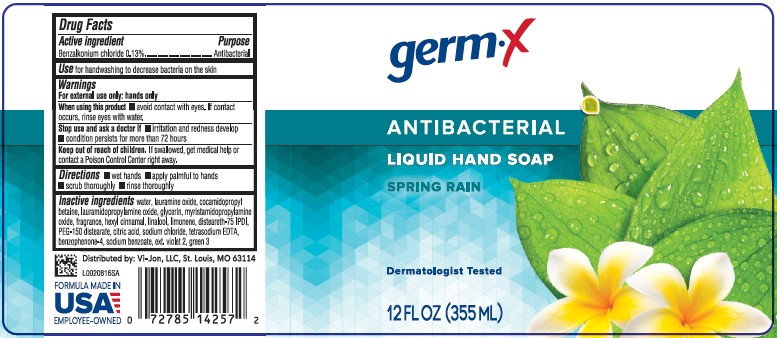 DRUG LABEL: Antibacterial Hand Wash Spring Rain
NDC: 83986-012 | Form: SOAP
Manufacturer: UpLift Brands, LLC
Category: otc | Type: HUMAN OTC DRUG LABEL
Date: 20250714

ACTIVE INGREDIENTS: BENZALKONIUM CHLORIDE 1.3 mg/1 mL
INACTIVE INGREDIENTS: WATER; LAURAMINE OXIDE; COCAMIDOPROPYL BETAINE; LAURAMIDOPROPYLAMINE OXIDE; GLYCERIN; MYRISTAMIDOPROPYLAMINE OXIDE; .ALPHA.-HEXYLCINNAMALDEHYDE; LINALOOL, (+/-)-; LIMONENE, (+)-; DISTEARETH-75 ISOPHORONE DIISOCYANATE; PEG-150 DISTEARATE; CITRIC ACID MONOHYDRATE; SODIUM CHLORIDE; EDETATE SODIUM; SULISOBENZONE; SODIUM BENZOATE; EXT. D&C VIOLET NO. 2; FD&C GREEN NO. 3

Germ-X D12.000/D12AB
Germ-X Antibacterial Hand Soap Spring Rain Scent

Active Ingredient

Benzalkonium chloride 0.13%

Purpose

Antibacterial

Use

for handwashing to decrease bacteria on the skin

Warnings

For external use only: hands only

When using this product

avoid contact with eyes. If contact occurs, rinse eyes with water.

Stop use and ask a doctor if

- irritation and redness develop
- condition persists for more than 72 hours

Keep out of reach of children.

If swallowed, get medical help or contact a Poison Control Center right away.

Directions

- wet hands
- apply palmful to hands
- scrub thoroughly
- rinse thoroughly

Inactive Ingredients

water, lauramine oxide, cocamidopropyl betaine, lauramidopropylamine oxide, glycerin, myristamidopropylamine oxide, fragrance, hexyl cinnamal, linalool, limonene, disteareth-75 IPDI, PEG-150 distearate, citric acid, sodium chloride, tetrasodium EDTA, benzophenone-4, sodium benzoate, ext. violet 2, green 3

Adverse reaction

Distributed by: Vi-Jon, LLC, St. Louis, MO 63114

FORMULA MADE IN USA

EMPLOYEE-OWNED

Principal panel display

germ-x

ANTIBACTERIAL

LIQUID HAND SOAP

SPRING RAIN

Dermatologist Tested

12 FL OZ (355 mL)